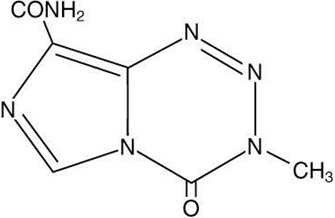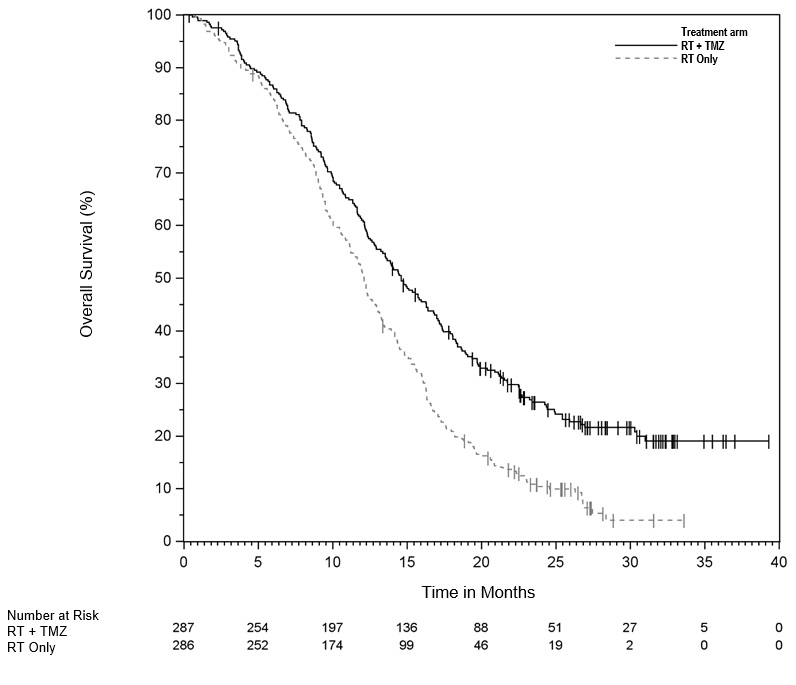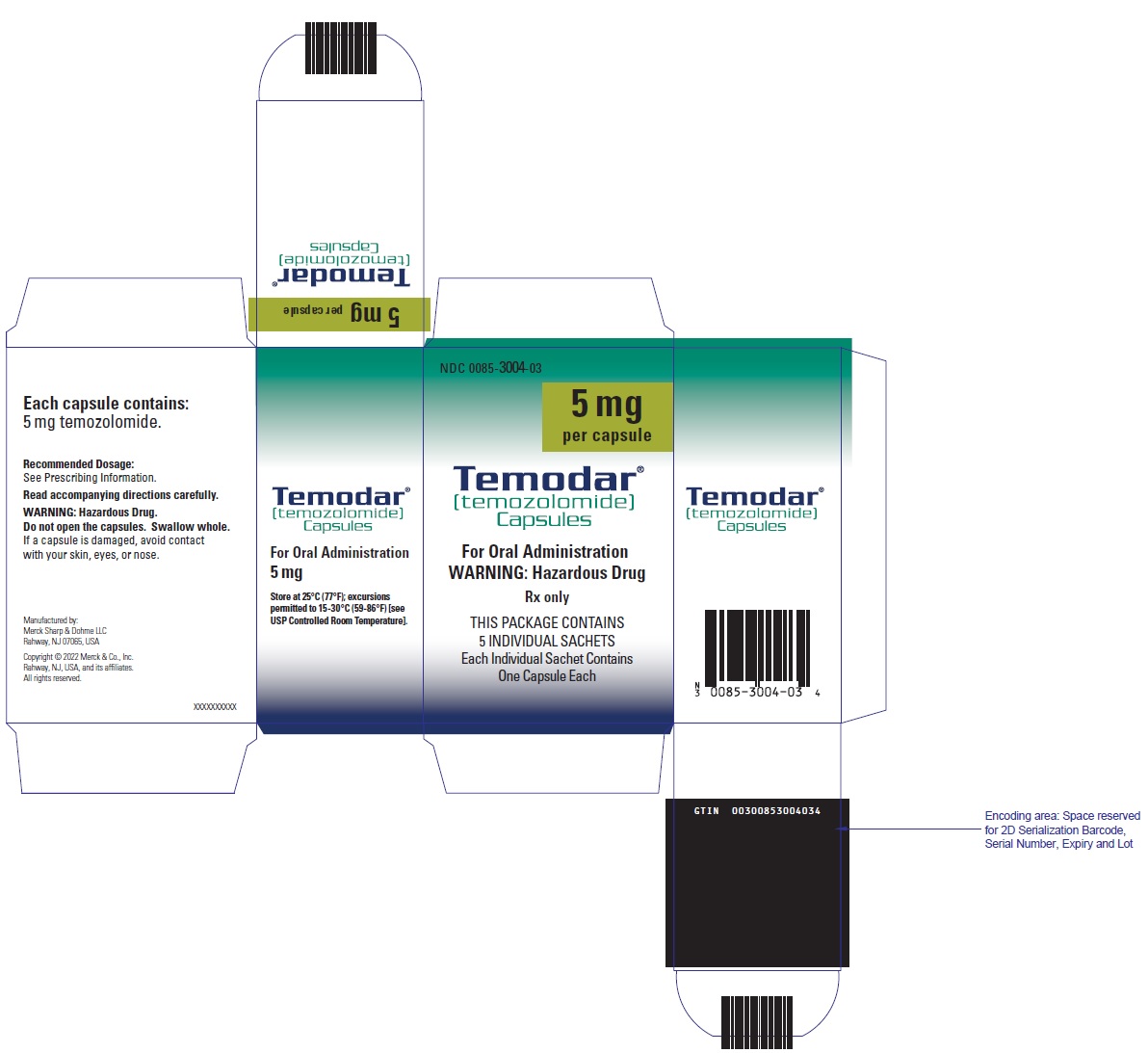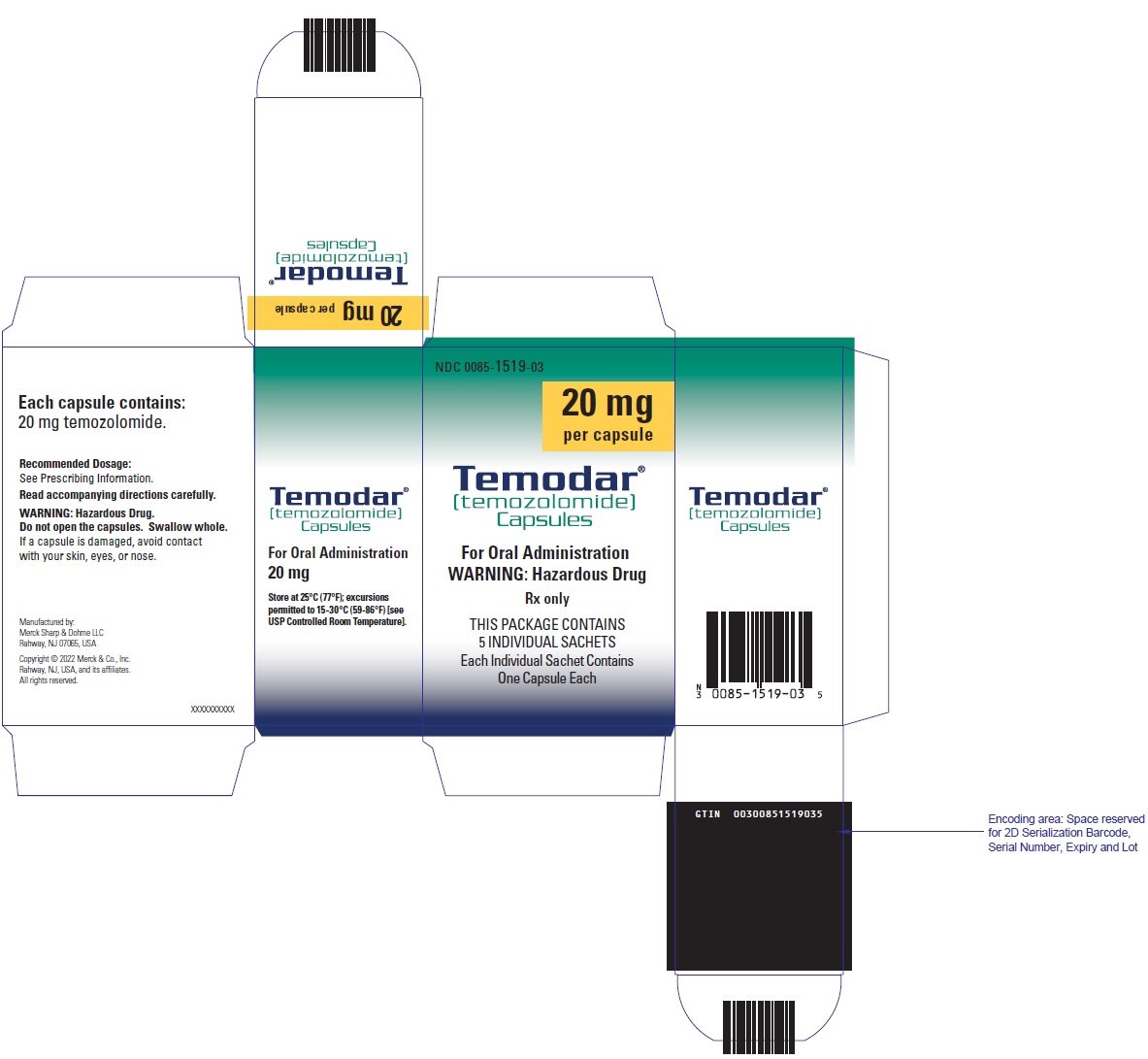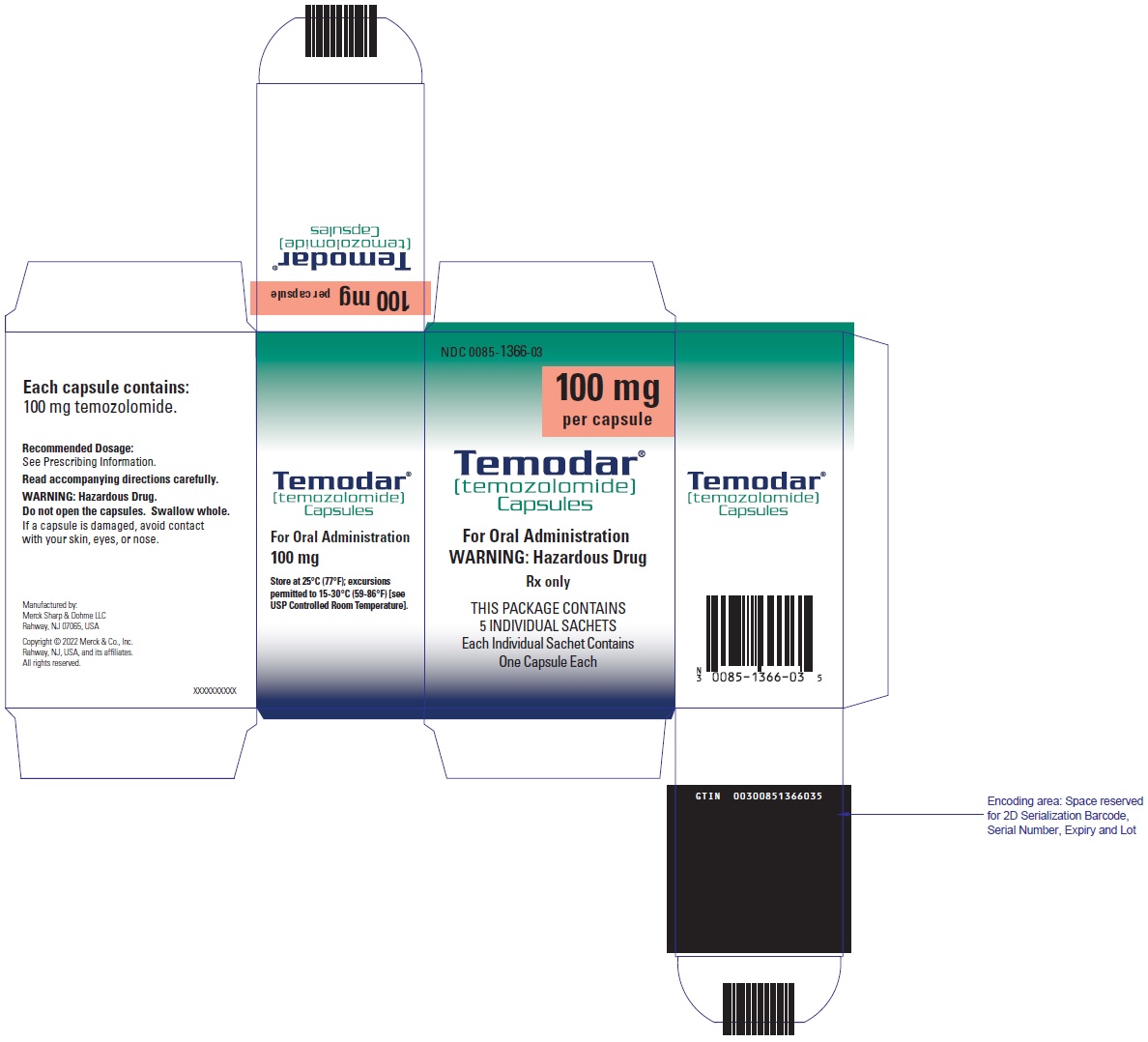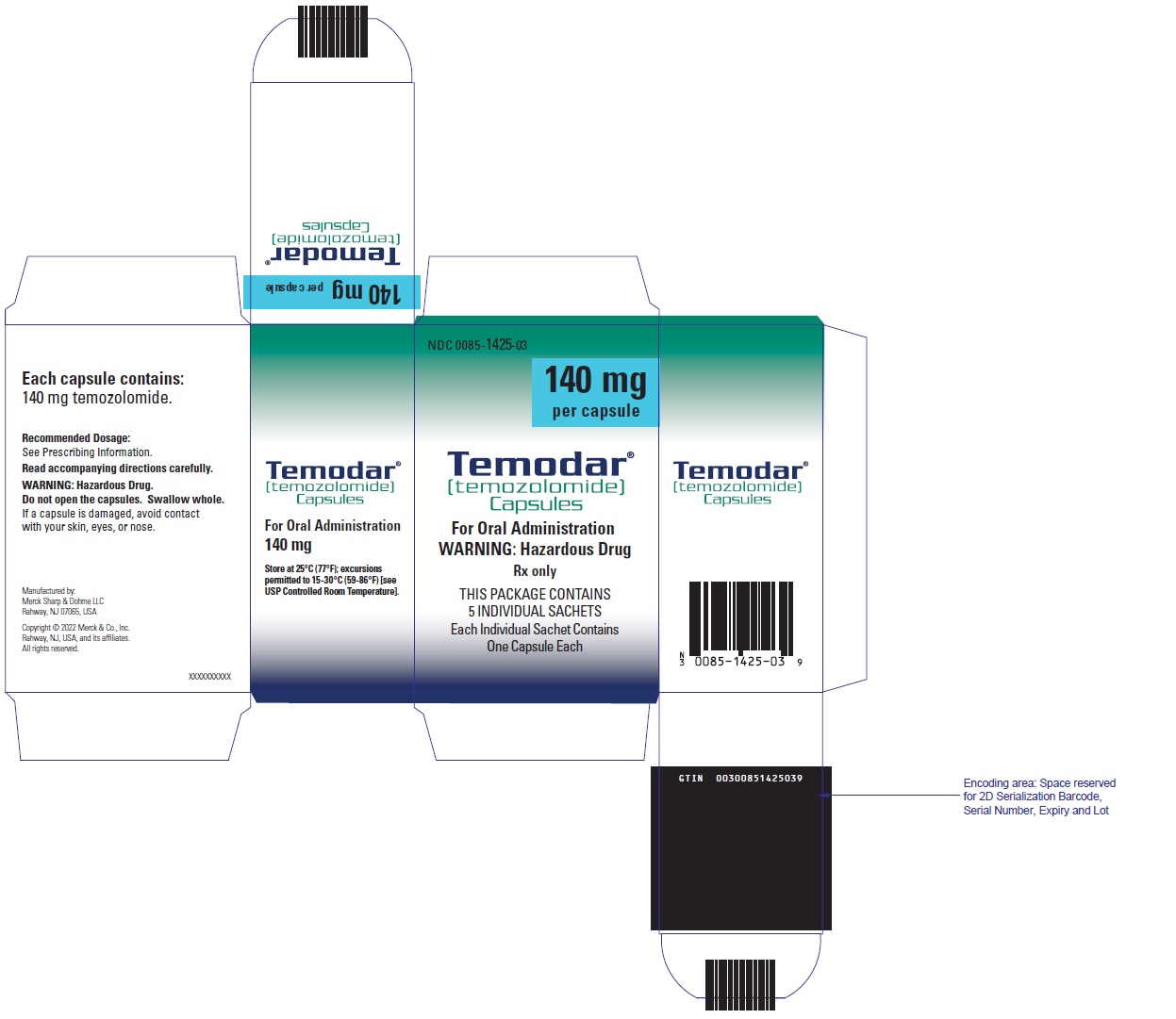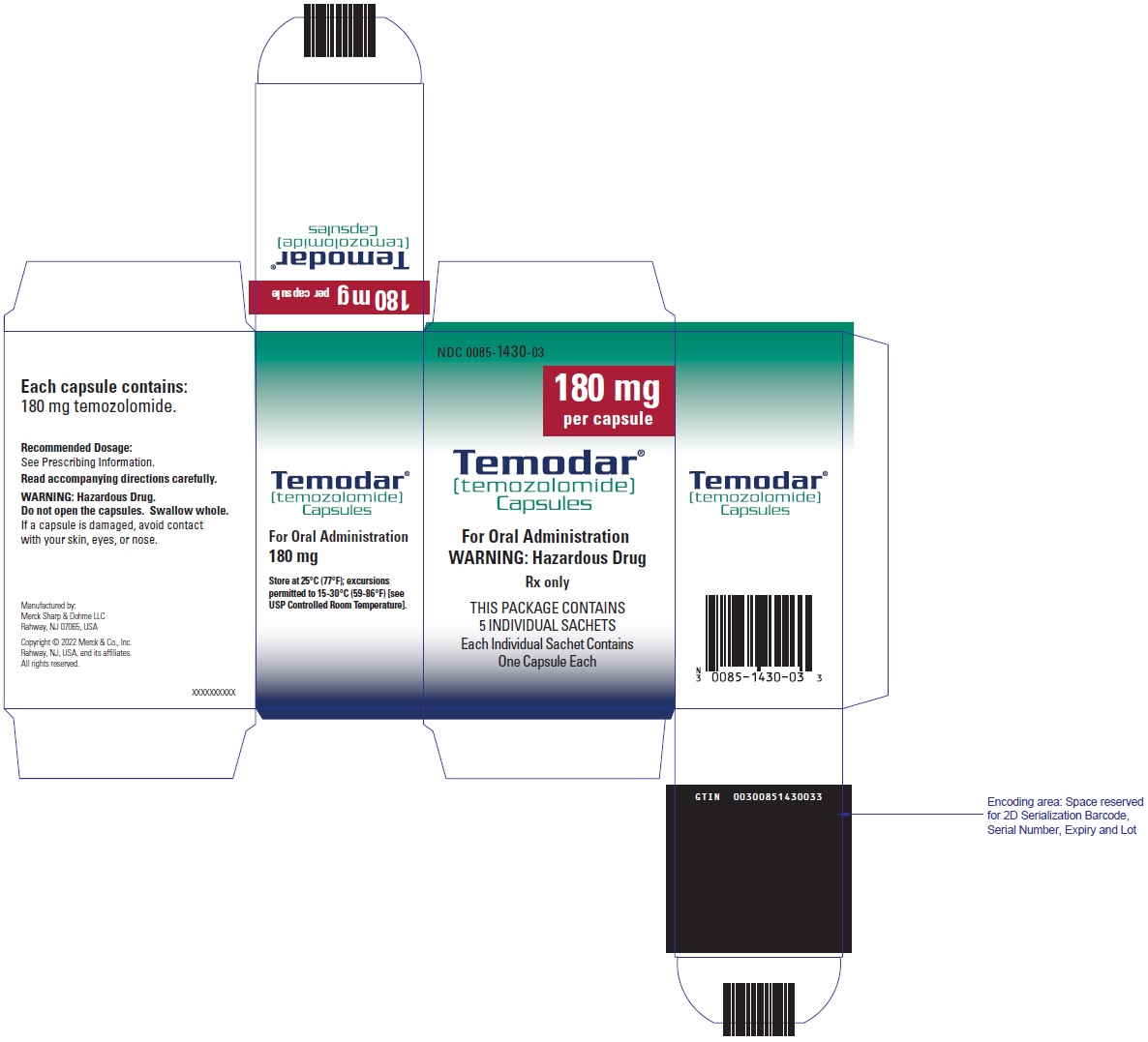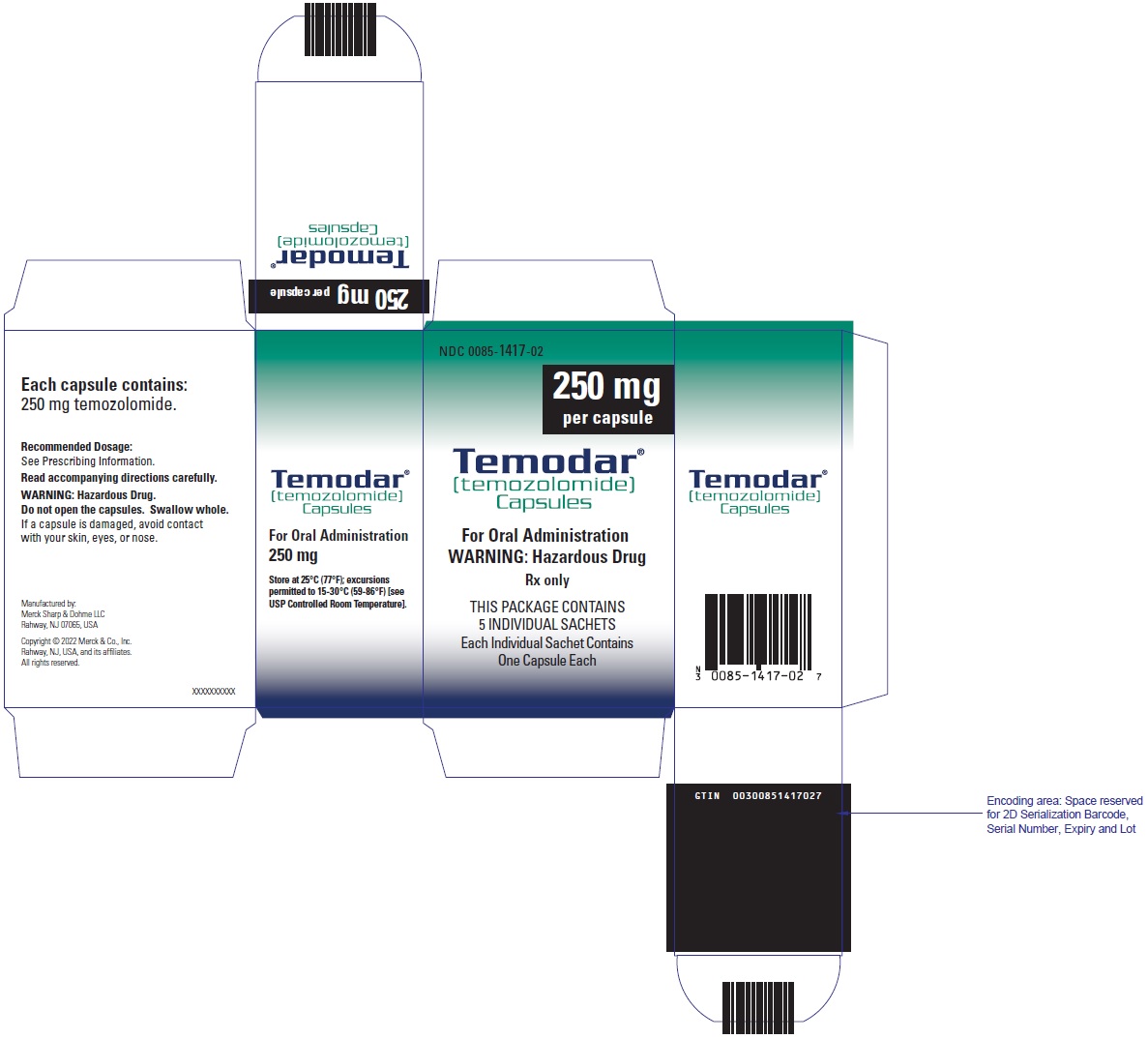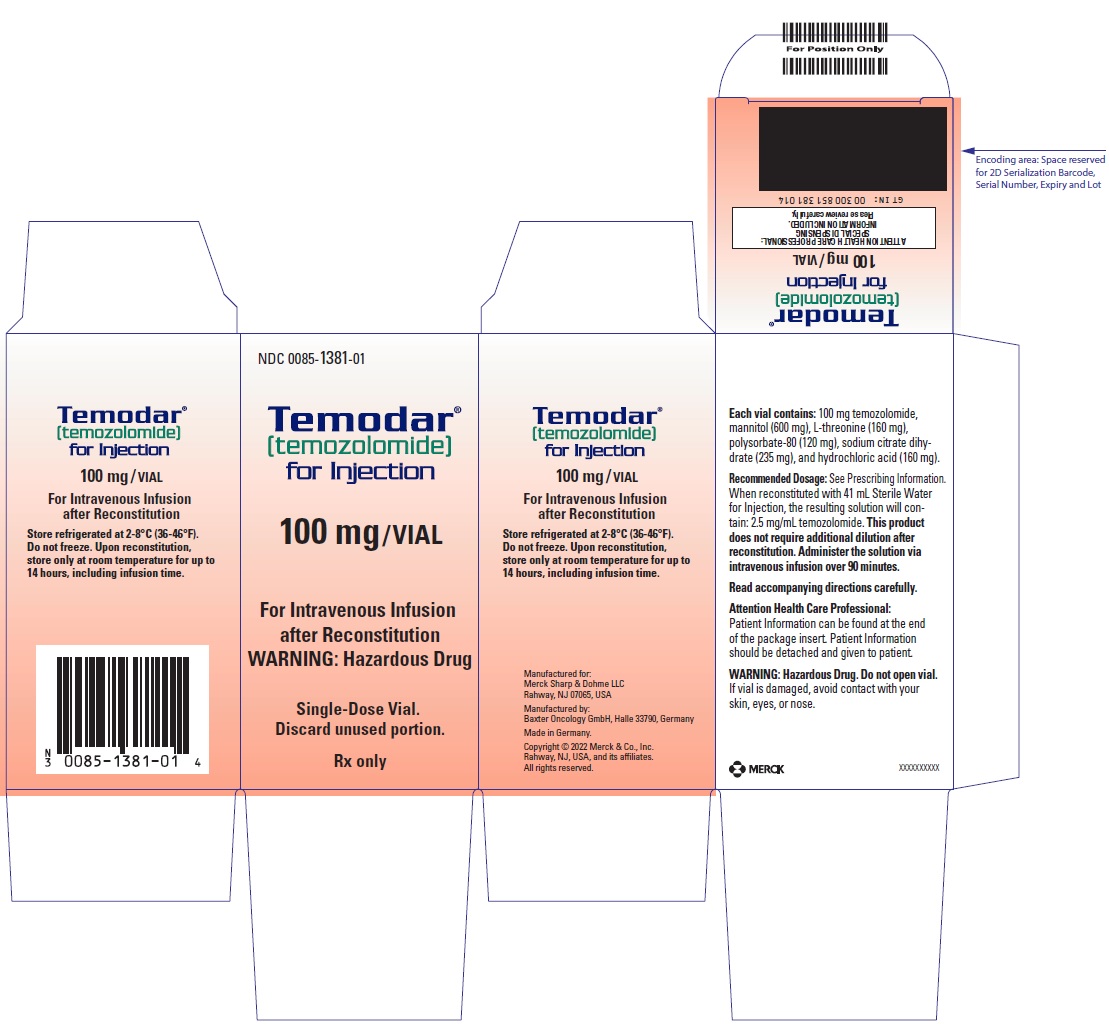 DRUG LABEL: TEMODAR
NDC: 0085-3004 | Form: CAPSULE
Manufacturer: Merck Sharp & Dohme LLC
Category: prescription | Type: HUMAN PRESCRIPTION DRUG LABEL
Date: 20241030

ACTIVE INGREDIENTS: Temozolomide 5 mg/1 1
INACTIVE INGREDIENTS: anhydrous lactose 132.8 mg/1 1; silicon dioxide 0.2 mg/1 1; sodium starch glycolate type A potato 7.5 mg/1 1; tartaric acid 1.5 mg/1 1; stearic acid 3 mg/1 1; shellac; alcohol; isopropyl alcohol; butyl alcohol; propylene glycol; water; ammonia; potassium hydroxide; ferric oxide red; GELATIN, UNSPECIFIED; titanium dioxide; ferric oxide yellow; sodium lauryl sulfate; FD&C Blue No. 2

HIGHLIGHTS OF PRESCRIBING INFORMATION

These highlights do not include all the information needed to use TEMODAR safely and effectively. See full prescribing information for TEMODAR.
TEMODAR® (temozolomide) capsules, for oral use
TEMODAR® (temozolomide) for injection, for intravenous use
Initial U.S. Approval: 1999

RECENT MAJOR CHANGES

Indications and Usage (1.2) | 9/2023
Dosage and Administration (2.1, 2.2, 2.3, 2.4) | 9/2023
Contraindications (4) | 9/2023
Warnings and Precautions (5.1, 5.2, 5.4, 5.5, 5.6) | 9/2023

1 INDICATIONS AND USAGE

TEMODAR is an alkylating drug indicated for the treatment of adults with:

- Newly diagnosed glioblastoma concomitantly with radiotherapy and then as maintenance treatment. (1.1)
- Anaplastic astrocytoma. (1.2)
  - Adjuvant treatment of adults with newly diagnosed anaplastic astrocytoma. (1.2)
  - Treatment of adults with refractory anaplastic astrocytoma. (1.2)

2 DOSAGE AND ADMINISTRATION

- Administer either orally or intravenously. (2.4)
- Newly Diagnosed Glioblastoma:
  - 75 mg/m^2 once daily for 42 to 49 days concomitant with focal radiotherapy followed by initial maintenance dose of 150 mg/m^2 once daily for Days 1 to 5 of each 28-day cycle for 6 cycles. May increase maintenance dose to 200 mg/m^2 for Cycles 2 to 6 based on toxicity. (2.1)
  - Provide Pneumocystis pneumonia (PCP) prophylaxis during concomitant phase and continue in patients who develop lymphopenia until resolution to Grade 1 or less. (2.1)
- Adjuvant Treatment of Newly Diagnosed Anaplastic Astrocytoma: Beginning 4 weeks after the end of radiotherapy, administer TEMODAR orally in a single dose on days 1-5 of a 28-day cycle for 12 cycles. The recommended dosage for Cycle 1 is 150 mg/m^2 per day and for Cycles 2 to 12 is 200 mg/m^2 if patient experienced no or minimal toxicity in Cycle 1. (2.2)
- Refractory Anaplastic Astrocytoma: Initial dose of 150 mg/m^2 once daily on Days 1 to 5 of each 28-day cycle. (2.2)

3 DOSAGE FORMS AND STRENGTHS

- Capsules: 5 mg, 20 mg, 100 mg, 140 mg, 180 mg, and 250 mg. (3)
- For injection: 100 mg as a lyophilized powder in single-dose vial for reconstitution. (3)

4 CONTRAINDICATIONS

- History of serious hypersensitivity to temozolomide or any other ingredients in TEMODAR and dacarbazine. (4)

5 WARNINGS AND PRECAUTIONS

- Myelosuppression: Monitor absolute neutrophil count (ANC) and platelet count prior to each cycle and during treatment. Geriatric patients and women have a higher risk of developing myelosuppression. (5.1, 8.5)
- Hepatotoxicity: Fatal and severe hepatotoxicity have been reported. Perform liver tests at baseline, midway through the first cycle, prior to each subsequent cycle, and approximately 2 to 4 weeks after the last dose of TEMODAR. (5.2)
- Pneumocystis Pneumonia (PCP): Closely monitor all patients, particularly those receiving steroids, for the development of lymphopenia and PCP. (5.3)
- Secondary Malignancies: Myelodysplastic syndrome and secondary malignancies, including myeloid leukemia, have been observed. (5.4)
- Embryo-Fetal Toxicity: Can cause fetal harm. Advise females of reproductive potential of the potential risk to a fetus and to use effective contraception. Advise male patients with pregnant partners or female partners of reproductive potential to use condoms. (5.5, 8.1, 8.3)
- Exposure to Opened Capsules: TEMODAR capsules should not be opened, chewed, or dissolved but should be swallowed whole with a glass of water. (5.6)

6 ADVERSE REACTIONS

- The most common adverse reactions (≥20%) are: alopecia, fatigue, nausea, vomiting, headache, constipation, anorexia, and convulsions. (6.1)
- The most common Grade 3 to 4 hematologic laboratory abnormalities (≥10%) in patients with anaplastic astrocytoma are: decreased lymphocytes, decreased platelets, decreased neutrophils, and decreased leukocytes. (6.1)

To report SUSPECTED ADVERSE REACTIONS, contact Merck Sharp & Dohme LLC at 1-877-888-4231 or FDA at 1-800-FDA-1088 or www.fda.gov/medwatch.

8 USE IN SPECIFIC POPULATIONS

- Lactation: Advise not to breastfeed. (8.2)

FULL PRESCRIBING INFORMATION

1 INDICATIONS AND USAGE

1.1 Newly Diagnosed Glioblastoma

TEMODAR is indicated for the treatment of adults with newly diagnosed glioblastoma, concomitantly with radiotherapy and then as maintenance treatment.

1.2 Anaplastic Astrocytoma

TEMODAR is indicated for the:

- adjuvant treatment of adults with newly diagnosed anaplastic astrocytoma;
- treatment of adults with refractory anaplastic astrocytoma.

2 DOSAGE AND ADMINISTRATION

2.1 Monitoring to Inform Dosage and Administration

Prior to dosing, withhold TEMODAR until patients have an absolute neutrophil count (ANC) of 1.5 x 10^9/L or greater and a platelet count of 100 x 10^9/L or greater.

For concomitant radiotherapy, obtain a complete blood count prior to initiation of treatment and weekly during treatment.

For the 28-day treatment cycles, obtain a complete blood count prior to treatment on Day 1 and on Day 22 of each cycle. Perform complete blood counts weekly until recovery if the ANC falls below 1.5 x 10^9/L and the platelet count falls below 100 x 10^9/L.

For concomitant use with focal radiotherapy, obtain a complete blood count weekly and as clinically indicated.

2.2 Recommended Dosage and Dosage Modifications for Newly Diagnosed Glioblastoma

Administer TEMODAR either orally or intravenously once daily for 42 to 49 consecutive days during the concomitant use phase with focal radiotherapy, and then once daily on Days 1 to 5 of each 28-day cycle for 6 cycles during the maintenance use phase.

Provide Pneumocystis pneumonia (PCP) prophylaxis during the concomitant use phase and continue in patients who develop lymphopenia until resolution to Grade 1 or less [see Warnings and Precautions (5.3)].

Concomitant Use Phase:

The recommended dosage of TEMODAR is 75 mg/m^2 either orally or intravenously once daily for 42 to 49 days in combination with focal radiotherapy. Focal radiotherapy includes the tumor bed or resection site with a 2 to 3 cm margin.

Other administration schedules have been used.

Obtain a complete blood count weekly. The recommended dosage modifications due to adverse reactions during concomitant use phase are provided in Table 1.

TABLE 1: Dosage Modifications Due to Adverse Reactions During Concomitant Use Phase
Adverse Reaction | Interruption | Discontinuation
Absolute Neutrophil Count | Withhold TEMODAR if ANC is greater than or equal to 0.5 × 10^9/L and less than 1.5 × 10^9/L. | Discontinue TEMODAR if ANC is less than 0.5 × 10^9/L.
Absolute Neutrophil Count | Resume TEMODAR at the same dose when ANC is greater than or equal to 1.5 × 10^9/L.
Platelet Count | Withhold TEMODAR if platelet count is greater than or equal to 10 × 10^9/L and less than 100 × 10^9/L. | Discontinue TEMODAR if platelet count is less than 10 × 10^9/L.
Platelet Count | Resume TEMODAR at the same dose when platelet count is greater than or equal to 100 × 10^9/L.
Non-hematological Adverse Reaction (except for alopecia, nausea, vomiting) | Withhold TEMODAR if Grade 2 adverse reaction occurs. | Discontinue TEMODAR if Grade 3 or 4 adverse reaction occurs.
Non-hematological Adverse Reaction (except for alopecia, nausea, vomiting) | Resume TEMODAR at the same dose when resolution to Grade 1 or less.

Single Agent Maintenance Use Phase:

Beginning 4 weeks after concomitant use phase completion, administer TEMODAR either orally or intravenously once daily on Days 1 to 5 of each 28-day cycle for 6 cycles. The recommended dosage of TEMODAR in the maintenance use phase is:

- Cycle 1: 150 mg/m^2 per day on days 1 to 5.
- Cycles 2 to 6: May increase to 200 mg/m^2 per day on days 1 to 5 before starting Cycle 2 if no dosage interruptions or discontinuations are required (Table 1). If the dose is not escalated at the onset of Cycle 2, do not increase the dose for Cycles 3 to 6.

Obtain a complete blood count on Day 22 and then weekly until the ANC is above 1.5 × 10^9/L and the platelet count is above 100 × 10^9/L. Do not start the next cycle until the ANC and platelet count exceed these levels.

The recommended dosage modifications due to adverse reactions during the maintenance use phase are provided in Table 2.

If TEMODAR is withheld, reduce the dose for the next cycle by 50 mg/m^2 per day. Permanently discontinue TEMODAR in patients who are unable to tolerate a dose of 100 mg/m^2 per day.

TABLE 2: Dosage Modifications Due to Adverse Reactions During Maintenance and Adjuvant Treatment
Adverse Reactions | Interruption and Dose Reduction | Discontinuation
Absolute Neutrophil Count | Withhold TEMODAR if ANC less than 1 × 10^9/L. | Discontinue TEMODAR if unable to tolerate a dose of 100 mg/m^2 per day.
Absolute Neutrophil Count | When ANC is above 1.5 × 10^9/L, resume TEMODAR at reduced dose for the next cycle.
Platelet Count | Withhold TEMODAR if platelet less than 50 × 10^9/L. | Discontinue TEMODAR if unable to tolerate a dose of 100 mg/m^2 per day.
Platelet Count | When platelet count is above 100 × 10^9/L, resume TEMODAR at reduced dose for the next cycle.
Nonhematological Adverse Reactions (except for alopecia, nausea, vomiting) | Withhold TEMODAR if Grade 3 adverse reaction occurs. | Discontinue TEMODAR if recurrent Grade 3 adverse reaction occurs after dose reduction, if Grade 4 adverse reaction occurs, or if unable to tolerate a dose of 100 mg/m^2 per day.
Nonhematological Adverse Reactions (except for alopecia, nausea, vomiting) | When resolved to Grade 1 or less, resume TEMODAR at reduced dose for the next cycle.

2.3 Recommended Dosage and Dosage Modifications for Anaplastic Astrocytoma

Adjuvant Treatment of Newly Diagnosed Anaplastic Astrocytoma

Beginning 4 weeks after the end of radiotherapy, administer TEMODAR orally in a single dose on days 1 to 5 of a 28-day cycle for 12 cycles. The recommended dosage of TEMODAR is:

- Cycle 1: 150 mg/m^2 per day on days 1 to 5.
- Cycles 2 to 12: 200 mg/m^2 per day on days 1 to 5 if patient experienced no or minimal toxicity in Cycle 1. If the dose was not escalated at the onset of Cycle 2, do not increase the dose during Cycles 3 to 6.

The recommended complete blood count testing and dosage modifications due to adverse reactions during adjuvant treatment are provided above and in Table 2 [see Dosage and Administration (2.2)].

Refractory Anaplastic Astrocytoma

The recommended initial dosage of TEMODAR is 150 mg/m^2 once daily on Days 1 to 5 of each 28-day cycle. Increase the TEMODAR dose to 200 mg/m^2 per day if the following conditions are met at the nadir and on Day 1 of the next cycle:

- ANC is greater than or equal to 1.5 × 10^9/L, and
- Platelet count is greater than or equal to 100 × 10^9/L.

Continue TEMODAR until disease progression or unacceptable toxicity.

Obtain a complete blood count on Day 22 and then weekly until the ANC is above 1.5 x 10^9/L and the platelet count is above 100 x 10^9/L. Do not start the next cycle until the ANC and platelet count exceed these levels.

If the ANC is less than 1 × 10^9/L or the platelet count is less than 50 × 10^9/L during any cycle, reduce the TEMODAR dose for the next cycle by 50 mg/m^2 per day. Permanently discontinue TEMODAR in patients who are unable to tolerate a dose of 100 mg/m^2 per day.

2.4 Preparation and Administration

TEMODAR is a hazardous drug. Follow applicable special handling and disposal procedures.^1

TEMODAR capsules

Take TEMODAR at the same time each day. Administer TEMODAR consistently with respect to food (fasting vs. nonfasting) [see Clinical Pharmacology (12.3)]. To reduce nausea and vomiting, take TEMODAR on an empty stomach or at bedtime and consider antiemetic therapy prior to and following TEMODAR administration.

Swallow TEMODAR capsules whole with water. Advise patients not to open, chew, or dissolve the contents of the capsules [see Warnings and Precautions (5.6)].

If capsules are accidentally opened or damaged, take precautions to avoid inhalation or contact with the skin or mucous membranes. In case of powder contact, wash the affected area with water immediately.

TEMODAR for injection

Bring the vial to room temperature prior to reconstitution with Sterile Water for Injection.

Reconstitute the vial with 41 mL of Sterile Water for Injection to yield a TEMODAR solution with a concentration of 2.5 mg/mL temozolomide. Reconstituted TEMODAR is a clear solution and essentially free of visible particles.

Gently swirl vial. Do not shake.

Parenteral drug products should be inspected visually for particulate matter and discoloration prior to administration, whenever solution and container permit. Discard if particulate matter or discoloration is observed.

Do not further dilute the reconstituted solution.

Store reconstituted solution at room temperature (25°C [77°F]). Discard reconstituted solution if not used within 14 hours, including infusion time.

Withdraw up to 40 mL from each vial to make up the total dose and discard any unused portion. Transfer reconstituted solution from each vial into an empty 250 mL infusion bag.

Administer reconstituted solution using a pump over a period of 90 minutes. Administer TEMODAR by intravenous infusion only. Infusion over a shorter or longer period of time may result in suboptimal dosing. Flush the lines before and after each infusion. TEMODAR for injection may be administered in the same intravenous line with 0.9% Sodium Chloride injection only.

Because no data are available on the compatibility of TEMODAR for injection with other intravenous substances or additives, do not infuse other medications simultaneously through the same intravenous line.

3 DOSAGE FORMS AND STRENGTHS

- Capsules:
  - 5 mg: opaque white bodies with green caps. The capsule body is imprinted with two stripes, the dosage strength, and the Schering-Plough logo. The cap is imprinted with “TEMODAR.”
  - 20 mg: opaque white bodies with yellow caps. The capsule body is imprinted with two stripes, the dosage strength, and the Schering-Plough logo. The cap is imprinted with “TEMODAR.”
  - 100 mg: opaque white bodies with pink caps. The capsule body is imprinted with two stripes, the dosage strength, and the Schering-Plough logo. The cap is imprinted with “TEMODAR.”
  - 140 mg: opaque white bodies with blue caps. The capsule body is imprinted with two stripes, the dosage strength, and the Schering-Plough logo. The cap is imprinted with “TEMODAR.”
  - 180 mg: opaque white bodies with orange caps. The capsule body is imprinted with two stripes, the dosage strength, and the Schering-Plough logo. The cap is imprinted with “TEMODAR.”
  - 250 mg: opaque white bodies with white caps. The capsule body is imprinted with two stripes, the dosage strength, and the Schering-Plough logo. The cap is imprinted with “TEMODAR.”
- For injection: 100 mg white to light tan or light pink lyophilized powder for reconstitution in a single-dose vial.

4 CONTRAINDICATIONS

TEMODAR is contraindicated in patients with a history of serious hypersensitivity reactions to:

- temozolomide or any other ingredients in TEMODAR; and
- dacarbazine, since both temozolomide and dacarbazine are metabolized to the same active metabolite 5-(3-methyltriazen-1-yl)-imidazole-4-carboxamide.

Reactions to TEMODAR have included anaphylaxis [see Adverse Reactions (6.2)].

5 WARNINGS AND PRECAUTIONS

5.1 Myelosuppression

Myelosuppression, including pancytopenia, leukopenia, and anemia, some with fatal outcomes, have occurred with TEMODAR [see Adverse Reactions (6.1, 6.2)].

In MK-7365-006, myelosuppression usually occurred during the first few cycles of therapy and was generally not cumulative. The median nadirs occurred at 26 days for platelets (range: 21 to 40 days) and 28 days for neutrophils (range: 1 to 44 days). Approximately 10% of patients required hospitalization, blood transfusion, or discontinuation of therapy due to myelosuppression. Geriatric patients and women have been shown in clinical trials to have a higher risk of developing myelosuppression.

Obtain a complete blood count and monitor ANC and platelet counts before initiation of treatment and as clinically indicated during treatment. When TEMODAR is used in combination with radiotherapy, obtain a complete blood count prior to initiation of treatment, weekly during treatment, and as clinically indicated [see Dosage and Administration (2.1, 2.2, 2.3)].

For severe myelosuppression, withhold TEMODAR and then resume at same or reduced dose, or permanently discontinue, based on occurrence [see Dosage and Administration (2.1, 2.2, 2.3)].

5.2 Hepatotoxicity

Fatal and severe hepatotoxicity have been reported in patients receiving TEMODAR. Perform liver tests at baseline, midway through the first cycle, prior to each subsequent cycle, and approximately two to four weeks after the last dose of TEMODAR.

5.3 Pneumocystis Pneumonia

Pneumocystis pneumonia (PCP) has been reported in patients receiving TEMODAR. The risk of PCP is increased in patients receiving steroids or with longer treatment regimens of TEMODAR.

For patients with newly diagnosed glioblastoma, provide PCP prophylaxis for all patients during the concomitant phase. Continue PCP prophylaxis in patients who experience lymphopenia, until resolution to Grade 1 or less [see Dosage and Administration (2.1)].

Monitor all patients receiving TEMODAR for the development of lymphopenia and PCP.

5.4 Secondary Malignancies

The incidence of secondary malignancies is increased in patients treated with TEMODAR-containing regimens. Cases of myelodysplastic syndrome and secondary malignancies, including myeloid leukemia, have been observed following TEMODAR administration.

5.5 Embryo-Fetal Toxicity

Based on findings from animal studies and its mechanism of action, TEMODAR can cause fetal harm when administered to a pregnant woman. Adverse developmental outcomes have been reported in both pregnant patients and pregnant partners of male patients. Oral administration of temozolomide to rats and rabbits during the period of organogenesis resulted in embryolethality and polymalformations at doses less than the maximum human dose based on body surface area.

Advise pregnant women and females of reproductive potential of the potential risk to a fetus. Advise females of reproductive potential to use effective contraception during treatment with TEMODAR and for 6 months after the last dose. Because of potential risk of genotoxic effects on sperm, advise male patients with female partners of reproductive potential to use condoms during treatment with TEMODAR and for 3 months after the last dose. Advise male patients not to donate semen during treatment with TEMODAR and for 3 months after the last dose [see Use in Specific Populations (8.1, 8.3)].

5.6 Exposure to Opened Capsules

Advise patients not to open, chew or dissolve the contents of the TEMODAR capsules. Swallow capsules whole with a glass of water. If a capsule becomes damaged, avoid contact of the powder contents with skin or mucous membranes. In case of powder contact, wash affected area with water immediately [see Dosage and Administration (2.4)]. If TEMODAR capsules must be opened or the contents must be dissolved, this should be done by a professional trained in safe handling of hazardous drugs using appropriate equipment and safety procedures.

6 ADVERSE REACTIONS

The following clinically significant adverse reactions are described elsewhere in the labeling:

- Myelosuppression [see Warnings and Precautions (5.1)]
- Hepatotoxicity [see Warnings and Precautions (5.2)]
- Pneumocystis Pneumonia [see Warnings and Precautions (5.3)]
- Secondary Malignancies [see Warnings and Precautions (5.4)]

6.1 Clinical Trials Experience

Because clinical trials are conducted under widely varying conditions, adverse reaction rates observed in the clinical trials of a drug cannot be directly compared to rates in the clinical trials of another drug and may not reflect the rates observed in practice.

Newly Diagnosed Glioblastoma

The safety of TEMODAR was evaluated in study MK-7365-051 [see Clinical Studies (14.1)].

Severe or life-threatening adverse reactions occurred in 49% of patients treated with TEMODAR; the most common were fatigue (13%), convulsions (6%), headache (5%), and thrombocytopenia (5%).

The most common adverse reactions (≥20%) in patients treated with TEMODAR were alopecia, fatigue, nausea, anorexia, headache, constipation, and vomiting.

Table 3 summarizes the adverse reactions in MK-7365-051.

TABLE 3: Adverse Reactions (≥10%) in Patients with Newly Diagnosed Glioblastoma
Adverse Reactions | Concomitant Use Phase |  |  |  | Maintenance Use Phase
Adverse Reactions | Radiation Therapy and TEMODAR N=288 [One patient who was randomized to radiation therapy-only arm received radiation therapy and TEMODAR.] |  | Radiation Therapy Alone N=285 |  | TEMODAR N=224
 | All Grades (%) | Grade ≥3 (%) | All Grades (%) | Grades ≥3 (%) | All Grades (%) | Grade ≥3 (%)
Skin and Subcutaneous Tissue
Alopecia | 69 | 0 | 63 | 0 | 55 | 0
Rash | 19 | 1 | 15 | 0 | 13 | 1
General
Fatigue | 54 | 7 | 49 | 5 | 61 | 9
Anorexia | 19 | 1 | 9 | <1 | 27 | 1
Headache | 19 | 2 | 17 | 4 | 23 | 4
Gastrointestinal System
Nausea | 36 | 1 | 16 | <1 | 49 | 1
Vomiting | 20 | <1 | 6 | <1 | 29 | 2
Constipation | 18 | 1 | 6 | 0 | 22 | 0
Diarrhea | 6 | 0 | 3 | 0 | 10 | 1
Central and Peripheral Nervous System
Convulsions | 6 | 3 | 7 | 3 | 11 | 3
NOS = not otherwise specified.
Note: Grade 5 (fatal) adverse reactions are included in the Grade ≥3 column.

Clinically relevant adverse reactions in <10% of patients are presented below:

Central & Peripheral Nervous System: memory impairment, confusion

Eye: vision blurred

Gastrointestinal System: stomatitis, abdominal pain

General: weakness, dizziness

Immune System: allergic reaction

Injury: radiation injury not otherwise specified

Musculoskeletal System: arthralgia

Platelet, Bleeding, & Clotting: thrombocytopenia

Psychiatric: insomnia

Respiratory System: coughing, dyspnea

Special Senses Other: taste perversion

Skin & Subcutaneous Tissue: dry skin, pruritus, erythema

When laboratory abnormalities and adverse reactions were combined, Grade 3 or Grade 4 neutrophil abnormalities including neutropenic reactions were observed in 8% of patients, and Grade 3 or Grade 4 platelet abnormalities including thrombocytopenic reactions were observed in 14% of patients.

Newly Diagnosed Anaplastic Astrocytoma

The safety of TEMODAR for the adjuvant treatment of adults with newly diagnosed anaplastic astrocytoma was derived from published literature [see Clinical Studies (14.2)]. The safety of TEMODAR for the adjuvant treatment of patients with newly diagnosed anaplastic astrocytoma was consistent with the known safety profile of TEMODAR.

Refractory Anaplastic Astrocytoma

The safety of TEMODAR was evaluated in study MK-7365-006 [see Clinical Studies (14.2)].

The most common adverse reactions (≥20%) were nausea, vomiting, headache, fatigue, constipation, and convulsions.

Tables 4 and 5 summarize the adverse reactions and hematological laboratory abnormalities in MK-7365-006.

TABLE 4: Adverse Reactions (≥10%) in Patients with Refractory Anaplastic Astrocytoma
Adverse Reactions | TEMODAR N=158
 | All Reactions (%) | Grades 3-4 (%)
Gastrointestinal System
Nausea | 53 | 10
Vomiting | 42 | 6
Constipation | 33 | 1
Diarrhea | 16 | 2
General
Headache | 41 | 6
Fatigue | 34 | 4
Asthenia | 13 | 6
Fever | 13 | 2
Central and Peripheral Nervous System
Convulsions | 23 | 5
Hemiparesis | 18 | 6
Dizziness | 12 | 1
Coordination abnormal | 11 | 1
Amnesia | 10 | 4
Insomnia | 10 | 0
Cardiovascular
Edema peripheral | 11 | 1
Resistance Mechanism
Infection viral | 11 | 0

Clinically relevant adverse reactions in <10% of patients are presented below:

Central and Peripheral Nervous System: paresthesia, somnolence, paresis, urinary incontinence, ataxia, dysphasia, convulsions local, gait abnormal, confusion

Endocrine: adrenal hypercorticism

Gastrointestinal System: abdominal pain, anorexia

General: back pain

Metabolic: weight increase

Musculoskeletal System: myalgia

Psychiatric: anxiety, depression

Reproductive Disorders: breast pain female

Respiratory System: upper respiratory tract infection, pharyngitis, sinusitis, coughing

Skin & Appendages: rash, pruritus

Urinary System: urinary tract infection, micturition increased frequency

Vision: diplopia, vision abnormal [This term includes blurred vision; visual deficit; vision changes; and vision troubles.]

TABLE 5: Grade 3 to 4 Hematologic Laboratory Abnormalities That Worsened from Baseline in Patients with Refractory Anaplastic Astrocytoma
 | TEMODAR [Change from Grade 0 to 2 at baseline to Grade 3 or 4 during treatment.] , [Denominator range= 142, 158] (%)
Decreased lymphocytes | 55
Decreased platelets | 19
Decreased neutrophils | 14
Decreased leukocytes | 11
Decreased hemoglobin | 4

Hematological Toxicities for Advanced Gliomas

In clinical trial experience with 110 to 111 females and 169 to 174 males (depending on measurements), females experienced higher rates of Grade 4 neutropenia (ANC <0.5 × 10^9/L) and thrombocytopenia (<20 × 10^9/L) than males in the first cycle of therapy (12% vs. 5% and 9% vs. 3%, respectively).

In the entire safety database for which hematologic data exist (N=932), 7% (4/61) and 10% (6/63) of patients >70 years experienced Grade 4 neutropenia or thrombocytopenia in the first cycle, respectively. For patients ≤70 years, 7% (62/871) and 6% (48/879) experienced Grade 4 neutropenia or thrombocytopenia in the first cycle, respectively. Pancytopenia, leukopenia, and anemia also occurred.

Injection Site Reactions

Adverse reactions that were reported in 35 patients who received TEMODAR for injection were pain, irritation, pruritus, warmth, swelling, and erythema at infusion site; petechiae; and hematoma.

6.2 Postmarketing Experience

The following adverse reactions have been identified during post-approval use of TEMODAR. Because these reactions are reported voluntarily from a population of uncertain size, it is not always possible to reliably estimate their frequency or establish a causal relationship to the drug exposure.

Dermatologic: Toxic epidermal necrolysis and Stevens-Johnson syndrome.

Immune System: Hypersensitivity reactions, including anaphylaxis. Erythema multiforme, which resolved after discontinuation of TEMODAR and, in some cases, recurred upon rechallenge.

Hematopoietic: Prolonged pancytopenia, which may result in aplastic anemia and fatal outcomes.

Hepatobiliary: Fatal and severe hepatotoxicity, elevation of liver enzymes, hyperbilirubinemia, cholestasis, and hepatitis.

Infections: Serious opportunistic infections, including some cases with fatal outcomes, with bacterial, viral (primary and reactivated), fungal, and protozoan organisms.

Pulmonary: Interstitial pneumonitis, pneumonitis, alveolitis, and pulmonary fibrosis.

Endocrine: Diabetes insipidus.

8 USE IN SPECIFIC POPULATIONS

8.1 Pregnancy

Risk Summary

Based on findings from animal studies and its mechanism of action [see Clinical Pharmacology (12.1)], TEMODAR can cause fetal harm when administered to a pregnant woman. Available postmarketing reports describe cases of spontaneous abortions and congenital malformations, including polymalformations with central nervous system, facial, cardiac, skeletal, and genitourinary system anomalies with exposure to TEMODAR during pregnancy. These cases report similar adverse developmental outcomes to those observed in animal studies. Administration of TEMODAR to rats and rabbits during the period of organogenesis caused numerous external, internal, and skeletal malformations at doses less than the maximum human dose based on body surface area (see Data). Advise pregnant women of the potential risk to a fetus.

In the U.S. general population, the estimated background risk of major birth defects and miscarriage in clinically recognized pregnancies is 2% to 4% and 15% to 20%, respectively.

Data

Animal Data

Five consecutive days of oral administration of temozolomide at doses of 75 and 150 mg/m^2 (0.38 and 0.75 times the human dose of 200 mg/m^2) in rats and rabbits, respectively, during the period of organogenesis (Gestation Days 8-12) caused numerous malformations of the external and internal organs and skeleton in both species. In rabbits, temozolomide at the 150 mg/m^2 dose (0.75 times the human dose of 200 mg/m^2) caused embryolethality as indicated by increased resorptions.

8.2 Lactation

There are no data on the presence of TEMODAR or its metabolites in human milk, the effects on a breastfed child, or the effects on milk production. Because of the potential for serious adverse reactions, including myelosuppression from temozolomide in the breastfed children, advise women not to breastfeed during treatment with TEMODAR and for 1 week after the last dose.

8.3 Females and Males of Reproductive Potential

TEMODAR can cause fetal harm when administered to a pregnant woman [see Use in Specific Populations (8.1)].

Pregnancy Testing

Verify pregnancy status in females of reproductive potential prior to initiating TEMODAR [see Use in Specific Populations (8.1)].

Contraception

Females

Advise females of reproductive potential to use effective contraception during treatment with TEMODAR and for 6 months after the last dose.

Males

Because of the potential for embryofetal toxicity and genotoxic effects on sperm cells, advise male patients with pregnant partners or female partners of reproductive potential to use condoms during treatment with TEMODAR and for 3 months after the last dose [see Use in Specific Populations (8.1), Nonclinical Toxicology (13.1)].

Advise male patients not to donate semen during treatment with TEMODAR and for 3 months after the last dose.

Infertility

TEMODAR may impair male fertility [see Nonclinical Toxicology (13.1)]. Limited data from male patients show changes in sperm parameters during treatment with TEMODAR; however, no information is available on the duration or reversibility of these changes.

8.4 Pediatric Use

Safety and effectiveness of TEMODAR have not been established in pediatric patients. Safety and effectiveness of TEMODAR capsules were assessed, but not established, in 2 open-label studies in pediatric patients aged 3 to 18 years. In one study, 29 patients with recurrent brain stem glioma and 34 patients with recurrent high-grade astrocytoma were enrolled. In a second study conducted by the Children's Oncology Group (COG), 122 patients were enrolled, including patients with medulloblastoma/PNET (29), high grade astrocytoma (23), low grade astrocytoma (22), brain stem glioma (16), ependymoma (14), other CNS tumors (9), and non-CNS tumors (9). The adverse reaction profile in pediatric patients was similar to adults.

8.5 Geriatric Use

In MK-7365-051, 15% of patients with newly diagnosed glioblastoma were 65 years and older. This study did not include sufficient numbers of patients aged 65 years and older to determine differences in effectiveness from younger patients. No overall differences in safety were observed between patients ≥65 years and younger patients.

The CATNON trial did not include sufficient numbers of patients aged 65 years and older to determine differences in safety or effectiveness when compared to younger patients.

In MK-7365-006, 4% of patients with refractory anaplastic astrocytoma were 70 years and older. This study did not include sufficient numbers of patients aged 70 years and older to determine differences in effectiveness from younger patients. Patients 70 years and older had a higher incidence of Grade 4 neutropenia (25%) and Grade 4 thrombocytopenia (20%) in the first cycle of therapy than patients less than 70 years of age [see Warnings and Precautions (5.1), Adverse Reactions (6.1)].

In the entire safety database for which hematologic data exist (N=932), 7% (4/61) and 10% (6/63) of patients >70 years experienced Grade 4 neutropenia or thrombocytopenia in the first cycle, respectively. For patients ≤70 years, 7% (62/871) and 6% (48/879) experienced Grade 4 neutropenia or thrombocytopenia in the first cycle, respectively. Pancytopenia, leukopenia, and anemia also occurred.

8.6 Renal Impairment

No dosage adjustment is recommended for patients with creatinine clearance (CLcr) of 36 to 130 mL/min/m^2 [see Clinical Pharmacology (12.3)]. The recommended dose of TEMODAR has not been established for patients with severe renal impairment (CLcr <36 mL/min/m^2) or for patients with end-stage renal disease on dialysis.

8.7 Hepatic Impairment

No dosage adjustment is recommended for patients with mild to moderate hepatic impairment (Child Pugh class A and B) [see Clinical Pharmacology (12.3)]. The recommended dose of TEMODAR has not been established for patients with severe hepatic impairment (Child-Pugh class C).

10 OVERDOSAGE

Dose-limiting toxicity was myelosuppression and was reported with any dose but is expected to be more severe at higher doses. An overdose of 2000 mg per day for 5 days was taken by one patient and the adverse reactions reported were pancytopenia, pyrexia, multi-organ failure, and death. There are reports of patients who have taken more than 5 days of treatment (up to 64 days), with adverse reactions reported including myelosuppression, which in some cases was severe and prolonged, and infections and resulted in death. In the event of an overdose, monitor complete blood count and provide supportive measures as necessary.

11 DESCRIPTION

Temozolomide is an alkylating drug. The chemical name of temozolomide is 3,4-dihydro-3-methyl-4-oxoimidazo[5,1-d]-as-tetrazine-8-carboxamide. The structural formula of temozolomide is:

The material is a white to light tan or light pink powder with a molecular formula of C6H6N6O2 and a molecular weight of 194.15. The molecule is stable at acidic pH (<5) and labile at pH >7; hence TEMODAR can be administered orally and intravenously. The prodrug, temozolomide, is rapidly hydrolyzed to the active 5-(3-methyltriazen-1-yl) imidazole-4-carboxamide (MTIC) at neutral and alkaline pH values, with hydrolysis taking place even faster at alkaline pH.

TEMODAR capsules

TEMODAR (temozolomide) capsules for oral use contains either 5 mg, 20 mg, 100 mg, 140 mg, 180 mg, or 250 mg of temozolomide. The inactive ingredients are as follows:

- TEMODAR 5 mg: lactose anhydrous (132.8 mg), colloidal silicon dioxide (0.2 mg), sodium starch glycolate (7.5 mg), tartaric acid (1.5 mg), and stearic acid (3 mg).
- TEMODAR 20 mg: lactose anhydrous (182.2 mg), colloidal silicon dioxide (0.2 mg), sodium starch glycolate (11 mg), tartaric acid (2.2 mg), and stearic acid (4.4 mg).
- TEMODAR 100 mg: lactose anhydrous (175.7 mg), colloidal silicon dioxide (0.3 mg), sodium starch glycolate (15 mg), tartaric acid (3 mg), and stearic acid (6 mg).
- TEMODAR 140 mg: lactose anhydrous (246 mg), colloidal silicon dioxide (0.4 mg), sodium starch glycolate (21 mg), tartaric acid (4.2 mg), and stearic acid (8.4 mg).
- TEMODAR 180 mg: lactose anhydrous (316.3 mg), colloidal silicon dioxide (0.5 mg), sodium starch glycolate (27 mg), tartaric acid (5.4 mg), and stearic acid (10.8 mg).
- TEMODAR 250 mg: lactose anhydrous (154.3 mg), colloidal silicon dioxide (0.7 mg), sodium starch glycolate (22.5 mg), tartaric acid (9 mg), and stearic acid (13.5 mg).

The body of the capsules is made of gelatin and is opaque white. The cap is also made of gelatin, and the colors vary based on the dosage strength. The capsule body and cap are imprinted with pharmaceutical branding ink, which contains shellac, dehydrated alcohol, isopropyl alcohol, butyl alcohol, propylene glycol, purified water, strong ammonia solution, potassium hydroxide, and ferric oxide.

- TEMODAR 5 mg: The green cap contains gelatin, titanium dioxide, iron oxide yellow, sodium lauryl sulfate, and FD&C Blue #2.
- TEMODAR 20 mg: The yellow cap contains gelatin, sodium lauryl sulfate, and iron oxide yellow.
- TEMODAR 100 mg: The pink cap contains gelatin, titanium dioxide, sodium lauryl sulfate, and iron oxide red.
- TEMODAR 140 mg: The blue cap contains gelatin, sodium lauryl sulfate, and FD&C Blue #2.
- TEMODAR 180 mg: The orange cap contains gelatin, iron oxide red, iron oxide yellow, titanium dioxide, and sodium lauryl sulfate.
- TEMODAR 250 mg: The white cap contains gelatin, titanium dioxide, and sodium lauryl sulfate.

TEMODAR for injection

TEMODAR (temozolomide) for injection is for intravenous use. Each single-dose vial contains 100 mg of sterile and pyrogen-free lyophilized powder. The inactive ingredients are: mannitol (600 mg), L-threonine (160 mg), polysorbate 80 (120 mg), sodium citrate dihydrate (235 mg), and hydrochloric acid (160 mg).

12 CLINICAL PHARMACOLOGY

12.1 Mechanism of Action

Temozolomide is not directly active but undergoes rapid nonenzymatic conversion at physiologic pH to the reactive compound 5-(3-methyltriazen-1-yl)-imidazole-4-carboxamide (MTIC). The cytotoxicity of MTIC is thought to be primarily due to DNA alkylation, mainly at the O^6 and N^7 positions of guanine, which causes DNA double strand breaks and results in programmed cell death.

12.2 Pharmacodynamics

Temozolomide exposure-response relationships and the time course of pharmacodynamic response are unknown.

12.3 Pharmacokinetics

Following a single oral dose of 150 mg/m^2, the mean Cmax is 7.5 mcg/mL for temozolomide and 282 ng/mL for MTIC. The mean AUC is 23.4 mcg∙hr/mL for temozolomide and 864 ng∙hr/mL for MTIC.

Following a single 90-minute intravenous infusion of 150 mg/m^2, the mean Cmax is 7.3 mcg/mL for temozolomide and 276 ng/mL for MTIC. The mean AUC is 24.6 mcg∙hr/mL for temozolomide and 891 ng∙hr/mL for MTIC.

Temozolomide exhibits linear kinetics over the therapeutic dosing range of 75 mg/m^2/day to 250 mg/m^2/day.

Absorption

The median Tmax is 1 hour.

Effect of Food

The mean temozolomide Cmax and AUC decreased by 32% and 9%, respectively, and median Tmax increased by 2-fold (from 1 to 2.25 hours) when TEMODAR capsules were administered after a modified high-fat breakfast (587 calories comprised of 1 fried egg, 2 strips of bacon, 2 slices of toast, 2 pats of butter, and 8 oz whole milk).

Distribution

Temozolomide has a mean (CV%) apparent volume of distribution of 0.4 L/kg (13%). The mean percent bound of drug-related total radioactivity is 15%.

Elimination

Clearance of temozolomide is approximately 5.5 L/hr/m^2 and the mean elimination half-life is 1.8 hours.

Metabolism

Temozolomide is spontaneously hydrolyzed at physiologic pH to the active species, MTIC and to temozolomide acid metabolite. MTIC is further hydrolyzed to 5-amino-imidazole-4-carboxamide (AIC), which is known to be an intermediate in purine and nucleic acid biosynthesis, and to methylhydrazine, which is believed to be the active alkylating species. Cytochrome P450 enzymes play a minor role in the metabolism of temozolomide and MTIC. Relative to the AUC of temozolomide, the exposure to MTIC and AIC is 2.4% and 23%, respectively.

Excretion

Approximately 38% of the administered temozolomide total radioactive dose is recovered over 7 days: 38% in urine and 0.8% in feces. The majority of the recovered radioactivity in urine is unchanged temozolomide (6%), AIC (12%), temozolomide acid metabolite (2.3%), and unidentified polar metabolite(s) (17%).

Specific Populations

No clinically significant differences in the pharmacokinetics of temozolomide were observed based on age (range: 19 to 78 years), gender, smoking status (smoker vs. non-smoker), creatinine clearance (CLcr) of 36 to 130 mL/min/m^2, or mild to moderate hepatic impairment (Child Pugh class A and B). The pharmacokinetics of temozolomide has not been studied in patients with CLcr <36 mL/min/m^2, end-stage renal disease on dialysis, or severe hepatic impairment (Child-Pugh class C).

Drug Interaction Studies

Clinical Studies and Model-Informed Approaches

No clinically significant differences in the pharmacokinetics of temozolomide or MTIC were observed when co-administered with ranitidine.

No clinically significant differences in the clearance of temozolomide or MTIC were predicted when co-administered with the following drugs: valproic acid, dexamethasone, prochlorperazine, phenytoin, carbamazepine, ondansetron, histamine-2-receptor antagonists, or phenobarbital.

13 NONCLINICAL TOXICOLOGY

13.1 Carcinogenesis, Mutagenesis, Impairment of Fertility

Temozolomide is carcinogenic in rats at doses less than the maximum recommended human dose. Temozolomide induced mammary carcinomas in both males and females at doses 0.13 to 0.63 times the maximum human dose (25-125 mg/m^2) when administered orally on 5 consecutive days every 28 days for 6 cycles. Temozolomide also induced fibrosarcomas of the heart, eye, seminal vesicles, salivary glands, abdominal cavity, uterus, and prostate, carcinomas of the seminal vesicles, schwannomas of the heart, optic nerve, and harderian gland, and adenomas of the skin, lung, pituitary, and thyroid at doses 0.5 times the maximum daily dose. Mammary tumors were also induced following 3 cycles of temozolomide at the maximum recommended daily dose.

Temozolomide is a mutagen and a clastogen. In a reverse bacterial mutagenesis assay (Ames assay), temozolomide increased revertant frequency in the absence and presence of metabolic activation. Temozolomide was clastogenic in human lymphocytes in the presence and absence of metabolic activation.

Temozolomide impairs male fertility. Temozolomide caused syncytial cells/immature sperm formation at doses of 50 and 125 mg/m^2 (0.25 and 0.63 times the human dose of 200 mg/m^2) in rats and dogs, respectively, and testicular atrophy in dogs at 125 mg/m^2.

13.2 Animal Toxicology and/or Pharmacology

Toxicology studies in rats and dogs identified a low incidence of hemorrhage, degeneration, and necrosis of the retina at temozolomide doses equal to or greater than 125 mg/m^2 (0.63 times the human dose of 200 mg/m^2). These changes were most commonly seen at doses where mortality was observed.

14 CLINICAL STUDIES

14.1 Newly Diagnosed Glioblastoma

The efficacy of TEMODAR was evaluated in MK-7365-051 (NCT00006353), a randomized (1:1), multicenter, open-label trial. Eligible patients were required to have newly diagnosed glioblastoma. Patients were randomized to receive either radiation therapy alone or concomitant TEMODAR 75 mg/m^2 once daily starting the first day of radiation therapy and continuing until the last day of radiation therapy for 42 days (with a maximum of 49 days), followed by TEMODAR 150 mg/m^2 or 200 mg/m^2 once daily on Days 1 to 5 of each 28-day cycle, starting 4 weeks after the end of radiation therapy and continuing for 6 cycles. In both arms, focal radiation therapy was delivered as 60 Gy/30 fractions and included radiation to the tumor bed or resection site with a 2- to 3-cm margin. PCP prophylaxis was required during the concomitant phase regardless of lymphocyte count and continued until recovery of lymphocyte count to Grade 1 or less. The major efficacy outcome measure was overall survival.

A total of 573 patients were randomized, 287 to TEMODAR and radiation therapy and 286 to radiation therapy alone. At the time of disease progression, TEMODAR was administered as salvage therapy in 161 patients of the 282 (57%) in the radiation therapy alone arm and 62 patients of the 277 (22%) in the TEMODAR and radiation therapy arm.

The addition of concomitant and maintenance TEMODAR to radiation therapy for the treatment of patients with newly diagnosed glioblastoma showed a statistically significant improvement in overall survival compared to radiotherapy alone (Figure 1). The hazard ratio (HR) for overall survival was 0.63 (95% CI: 0.52, 0.75) with a log-rank P<0.0001 in favor of the TEMODAR arm. The median overall survival was 14.6 months in the TEMODAR arm and 12.1 months for radiation therapy alone arm.

FIGURE 1: Kaplan-Meier Curves for Overall Survival (ITT Population) in Patients with Newly Diagnosed Glioblastoma in MK-7365-051

14.2 Anaplastic Astrocytoma

Newly Diagnosed Anaplastic Astrocytoma

The efficacy of TEMODAR for the adjuvant treatment of newly diagnosed anaplastic astrocytoma was derived from studies of TEMODAR in the published literature. TEMODAR was evaluated in CATNON (NCT00626990), a randomized, open-label, multicenter trial, where the major efficacy outcome measure was overall survival.

Refractory Anaplastic Astrocytoma

The efficacy of TEMODAR was evaluated in Study MK-7365-006, a single-arm, multicenter trial. Eligible patients had anaplastic astrocytoma at first relapse and a baseline Karnofsky performance status (KPS) of 70 or greater. Patients had previously received radiation therapy and may also have previously received a nitrosourea with or without other chemotherapy. Fifty-four patients had disease progression on prior therapy with both a nitrosourea and procarbazine and their malignancy was considered refractory to chemotherapy (refractory anaplastic astrocytoma population). TEMODAR capsules were given on Days 1 to 5 of each 28-day cycle at a starting dose of 150 mg/m^2/day. If ANC was ≥1.5 × 10^9/L and platelet count was ≥100 × 10^9/L at the nadir and on Day 1 of the next cycle, the TEMODAR dose was increased to 200 mg/m^2/day. The major efficacy outcome measure was progression-free survival at 6 months and the additional efficacy outcome measures were overall survival and overall response rate.

In the refractory anaplastic astrocytoma population (n=54), the median age was 42 years (range: 19 to 76); 65% were male; and 72% had a KPS of >80. Sixty-three percent of patients had surgery other than a biopsy at the time of initial diagnosis. Of those patients undergoing resection, 73% underwent a subtotal resection and 27% underwent a gross total resection. Eighteen percent of patients had surgery at the time of first relapse. The median time from initial diagnosis to first relapse was 13.8 months (range: 4.2 months to 6.3 years).

In the refractory anaplastic astrocytoma population, the overall response rate (CR+PR) was 22% (12 of 54 patients) and the complete response rate was 9% (5 of 54 patients). The median duration of all responses was 50 weeks (range: 16 to 114 weeks) and the median duration of complete responses was 64 weeks (range: 52 to 114 weeks). In this population, progression-free survival at 6 months was 45% (95% CI: 31%, 58%) and progression-free survival at 12 months was 29% (95% CI: 16%, 42%). Median progression-free survival was 4.4 months. Overall survival at 6 months was 74% (95% CI: 62%, 86%) and 12-month overall survival was 65% (95% CI: 52%, 78%). Median overall survival was 15.9 months.

15 REFERENCES

1. “OSHA Hazardous Drugs.” OSHA. http://www.osha.gov/hazardous-drugs

16 HOW SUPPLIED/STORAGE AND HANDLING

TEMODAR is a hazardous drug. Follow applicable special handling and disposal procedures.^1

TEMODAR capsules

TEMODAR capsules are supplied in child-resistant sachets containing the following capsule strengths:

5 mg: opaque white bodies with green caps. The capsule body is imprinted with two stripes, the dosage strength, and the Schering-Plough logo. The cap is imprinted with “TEMODAR”. They are supplied as follows:

5-count – NDC 0085-3004-03
14-count – NDC 0085-3004-04

20 mg: opaque white bodies with yellow caps. The capsule body is imprinted with two stripes, the dosage strength, and the Schering-Plough logo. The cap is imprinted with “TEMODAR”. They are supplied as follows:

5-count – NDC 0085-1519-03
14-count – NDC 0085-1519-04

100 mg: opaque white bodies with pink caps. The capsule body is imprinted with two stripes, the dosage strength, and the Schering-Plough logo. The cap is imprinted with “TEMODAR”. They are supplied as follows:

5-count – NDC 0085-1366-03
14-count – NDC 0085-1366-04

140 mg: opaque white bodies with blue caps. The capsule body is imprinted with two stripes, the dosage strength, and the Schering-Plough logo. The cap is imprinted with “TEMODAR”. They are supplied as follows:

5-count – NDC 0085-1425-03
14-count – NDC 0085-1425-04

180 mg: opaque white bodies with orange caps. The capsule body is imprinted with two stripes, the dosage strength, and the Schering-Plough logo. The cap is imprinted with “TEMODAR”. They are supplied as follows:

5-count – NDC 0085-1430-03
14-count – NDC 0085-1430-04

250 mg: opaque white bodies with white caps. The capsule body is imprinted with two stripes, the dosage strength, and the Schering-Plough logo. The cap is imprinted with “TEMODAR”. They are supplied as follows:

5-count – NDC 0085-1417-02

STORAGE AND HANDLING

Store TEMODAR Capsules at 25°C (77°F); excursions permitted to 15°C to 30°C (59°F to 86°F) [see USP Controlled Room Temperature].

TEMODAR for injection

TEMODAR for injection is supplied in single-dose glass vials containing 100 mg temozolomide. The lyophilized powder is white to light tan or light pink.

NDC 0085-1381-01

STORAGE AND HANDLING

Store TEMODAR for injection refrigerated at 2°C to 8°C (36°F to 46°F).

17 PATIENT COUNSELING INFORMATION

Advise the patient to read the FDA-approved patient labeling (Patient Information).

Myelosuppression

Inform patients that TEMODAR can cause low blood cell counts and the need for frequent monitoring of blood cell counts. Advise patients to contact their healthcare provider immediately for bleeding, fever, or other signs of infection [see Warnings and Precautions (5.1)].

Hepatotoxicity

Advise patients of the increased risk of hepatotoxicity and to contact their healthcare provider immediately for signs or symptoms of hepatotoxicity. Inform patients that they will have periodic liver enzyme tests during treatment and following the last dose of TEMODAR [see Warnings and Precautions (5.2)].

Pneumocystis Pneumonia

Advise patients of the increased risk of Pneumocystis pneumonia and to contact their healthcare provider immediately for new or worsening pulmonary symptoms. Inform patients that prophylaxis for Pneumocystis pneumonia may be needed [see Dosage and Administration (2.1), Warnings and Precautions (5.3)].

Secondary Malignancies

Advise patients of the increased risk of myelodysplastic syndrome and secondary malignancies [see Warnings and Precautions (5.4)].

Exposure to Opened Capsules

Advise patient to not open, chew, or dissolve the capsules. If capsules are accidentally opened or damaged, advise patients to take rigorous precautions with capsule contents to avoid inhalation or contact with the skin or mucous membranes [see Warnings and Precautions (5.6)]. In case of powder contact, wash the affected area with water immediately [see Dosage and Administration (2.4)].

Embryo-Fetal Toxicity

Advise pregnant women and females of reproductive potential of the potential risk to a fetus. Advise females to inform their healthcare provider of a known or suspected pregnancy [see Warnings and Precautions (5.5), Use in Specific Populations (8.1)].

Advise females of reproductive potential to use effective contraception during treatment with TEMODAR and for 6 months after the last dose [see Use in Specific Populations (8.3)].

Advise male patients with pregnant partners or female partners of reproductive potential to use condoms during treatment with TEMODAR and for 3 months after the last dose [see Use in Specific Populations (8.3), Nonclinical Toxicology (13.1)].

Advise male patients not to donate semen during treatment with TEMODAR and for 3 months after the last dose [see Use in Specific Populations (8.3), Nonclinical Toxicology (13.1)].

Lactation

Advise women not to breastfeed during treatment with TEMODAR and for 1 week after the last dose [see Use in Specific Populations (8.2)].

Infertility

Advise males of reproductive potential that TEMODAR may impair fertility [see Use in Specific Populations (8.3), Nonclinical Toxicology (13.1)].

Distributed by: Merck Sharp & Dohme LLC
Rahway, NJ 07065, USA

For patent information: www.msd.com/research/patent

Copyright © 1999-2023 Merck & Co., Inc., Rahway, NJ, USA, and its affiliates.
All rights reserved.

uspi-mk7365-mtl-2309r024

Patient Information

TEMODAR® (tem-o-dar)
(temozolomide)
capsules

TEMODAR® (tem-o-dar)
(temozolomide)
for injection

What is TEMODAR?

TEMODAR is a prescription medicine used to treat adults with certain brain cancer tumors.

It is not known if TEMODAR is safe and effective in children.

Do not take TEMODAR if you:

- have had an allergic reaction to temozolomide or any of the other ingredients in TEMODAR. See the end of this leaflet for a list of ingredients in TEMODAR. Symptoms of an allergic reaction with TEMODAR may include: a red itchy rash, or a severe allergic reaction, such as trouble breathing, swelling of the face, throat, or tongue, or severe skin reaction. If you are not sure, ask your healthcare provider.
- have had an allergic reaction to dacarbazine (DTIC), another cancer medicine.

Before taking or receiving TEMODAR, tell your healthcare provider about all of your medical conditions, including if you:

- have kidney problems
- have liver problems
- are pregnant or plan to become pregnant. TEMODAR can harm your unborn baby and cause birth defects.
  Females who can become pregnant:
  - You should not become pregnant during treatment with TEMODAR.
  - You should use an effective form of birth control (contraception) during treatment and for 6 months after your last dose of TEMODAR.
  - Your healthcare provider should do a pregnancy test to make sure that you are not pregnant before you start taking TEMODAR.
  - Tell your healthcare provider right away if you become pregnant or think you may be pregnant during treatment with TEMODAR.
  Males with a female partner who is pregnant or who can become pregnant:
  - Use a condom for birth control (contraception) during treatment and for 3 months after taking your last dose of TEMODAR.
  - Do not donate semen during treatment and for 3 months after your last dose of TEMODAR.
- are breastfeeding or plan to breastfeed. It is not known if TEMODAR passes into your breast milk. Do not breastfeed during treatment and for 1 week after your last dose of TEMODAR.

Tell your doctor about all the medicines you take, including prescription and non-prescription medicines, vitamins, and herbal supplements.

Know the medicines you take. Keep a list of them and show it to your healthcare provider and pharmacist when you get a new medicine.

How should I take TEMODAR?

TEMODAR may be taken 2 different ways:

- you may take TEMODAR by mouth as a capsule, or
- you may receive TEMODAR as an intravenous (IV) injection into your vein.
  Your healthcare provider will decide the best way for you to take TEMODAR.
- If your healthcare provider prescribes TEMODAR capsules for you, take the capsules exactly as prescribed.

There are 2 common dosing schedules for taking or receiving TEMODAR depending on the type of brain cancer tumor that you have.

- People with certain brain cancer tumors take or receive TEMODAR:
  - 1 time each day for 42 to 49 days in a row, along with receiving radiation treatment. This is 1 cycle of treatment.
    After this, your healthcare provider may prescribe 6 more cycles of TEMODAR as “maintenance” treatment. For each of these cycles, you take or receive TEMODAR 1 time each day for 5 days in a row and then you stop taking it for the next 23 days. This is a 28-day maintenance treatment cycle.

- People with certain other brain cancer tumors take or receive TEMODAR:
  - 1 time each day for 5 days in a row only, and then stop taking it for the next 23 days. This is 1 cycle of treatment (28 days).
  - Your healthcare provider will watch your progress on TEMODAR and decide how long you should take it.
- If your healthcare provider prescribes a treatment regimen that is different from the information in this leaflet, make sure you follow the instructions given to you by your healthcare provider.
- Your healthcare provider may change your dose of TEMODAR, or tell you to stop TEMODAR for a short period of time or permanently if you have certain side effects.
- Your healthcare provider will decide how many treatment cycles of TEMODAR that you will receive, depending on how you respond to and tolerate treatment.

TEMODAR capsules:

- Take TEMODAR capsules exactly as your healthcare provider tells you to.
- TEMODAR capsules contain a white capsule body with a color cap and the colors vary based on the dosage strength. Your healthcare provider may prescribe more than 1 strength of TEMODAR capsules for you, so it is important that you understand how to take your medicine the right way. Be sure that you understand exactly how many capsules you need to take on each day of your treatment, and what strengths to take. This may be different whenever you start a new cycle.
- Do not take more TEMODAR than prescribed.
- Talk to your healthcare provider or pharmacist before taking your dose if you are not sure how much TEMODAR to take. This will help to prevent taking too much TEMODAR and decrease your chances of getting serious side effects.
- Take each day's dose of TEMODAR capsules at one time, with a full glass of water.
- Take TEMODAR capsules at the same time each day.
- Take TEMODAR the same way each time, either with food or without food.
- Swallow TEMODAR capsules whole with water. Do not open, chew, or dissolve the contents of the capsules.
- If TEMODAR capsules are accidentally opened or damaged, be careful not to breathe in (inhale) the powder from the capsules or get the powder on your skin or mucous membranes (for example, in your nose or mouth). If contact with any of these areas happens, wash the area with water right away.
- To help reduce nausea and vomiting, try to take TEMODAR on an empty stomach or at bedtime. Your healthcare provider may prescribe medicine to help prevent or treat nausea, or other medicines to reduce side effects with TEMODAR.
- See your healthcare provider regularly to check your progress. Your healthcare provider will check you for side effects.
- If you take more TEMODAR than prescribed, call your healthcare provider or get emergency medical help right away.

TEMODAR for injection:

- You will receive TEMODAR as an infusion directly into your vein over about 90 minutes.
- Your healthcare provider may prescribe medicine to prevent or treat nausea, or other medicines to help relieve side effects with TEMODAR.
- For certain people taking or receiving TEMODAR, your healthcare provider may prescribe an antibiotic to prevent certain infections if you have certain white blood cell counts that are too low.

What are the possible side effects of TEMODAR?

TEMODAR can cause serious side effects, including:

- Decreased blood cell counts. TEMODAR can affect your bone marrow and cause you to have decreased blood cell counts. Decreased white blood cell count, red blood cell count and platelet count are common with TEMODAR but it can also be severe and lead to death. Some people need to be hospitalized or need to receive transfusions to treat their decreased blood cell counts.
  - Your healthcare provider will do blood tests regularly to check your blood cell counts before you start and during treatment with TEMODAR.
  - Your healthcare provider may need to change the dose of TEMODAR or when you get it depending on your blood cell counts.
  - People who are age 70 or older and women have a higher risk for developing decreased blood cell counts during treatment with TEMODAR.
- Liver problems. Liver problems can happen with TEMODAR and can sometimes be severe and lead to death. Your healthcare provider will do blood tests to check your liver function before you start taking TEMODAR, during treatment, and about 2 to 4 weeks after your last dose of TEMODAR.
- Pneumocystis pneumonia (PCP). PCP is an infection that people can get when their immune system is weak. TEMODAR decreases white blood cells, which makes your immune system weaker and can increase your risk of getting PCP.
  - People who are taking steroid medicines or who stay on TEMODAR for a longer period of time may have an increased risk of getting PCP infection.
  - Anyone who takes TEMODAR will be watched carefully by their healthcare provider for low blood cell counts and this infection.
  - Tell your healthcare provider if you have any of the following signs and symptoms of PCP infection: shortness of breath, or fever, chills, dry cough.
- Secondary Cancers. Blood problems such as myelodysplastic syndrome (MDS) and new cancers (secondary cancers), including a certain kind of leukemia, can happen in people who take TEMODAR. Your healthcare provider will monitor you for this.

Common side effects of TEMODAR include:

- hair loss
- feeling tired
- nausea and vomiting

- headache
- constipation
- loss of appetite
- convulsions

Additional side effects seen with TEMODAR for injection include:

- pain, irritation, itching, warmth, swelling, or redness at the site of infusion
- bruising or small red or purple spots under the skin

TEMODAR can affect fertility in males and may affect your ability to father a child. Talk with your healthcare provider if fertility is a concern for you.

Tell your healthcare provider about any side effect that bothers you or that does not go away.

These are not all the possible side effects of TEMODAR. For more information, ask your healthcare provider or pharmacist.

Call your doctor for medical advice about side effects. You may report side effects to FDA at 1-800-FDA-1088.

How should I store TEMODAR capsules?

- Store TEMODAR capsules at room temperature between 68°F to 77°F (20°C to 25°C).

Keep TEMODAR and all medicines out of the reach of children.

General information about the safe and effective use of TEMODAR.

Medicines are sometimes prescribed for purposes other than those listed in a Patient Information leaflet. Do not use TEMODAR for a condition for which it was not prescribed. Do not give TEMODAR to other people, even if they have the same symptoms that you have. It may harm them. You can ask your pharmacist or healthcare provider for information about TEMODAR that is written for health professionals.

What are the ingredients in TEMODAR?

TEMODAR capsules:

Active ingredient: temozolomide

Inactive ingredients: lactose anhydrous, colloidal silicon dioxide, sodium starch glycolate, tartaric acid, stearic acid.

The body of the capsules is made of gelatin and is opaque white. The cap is also made of gelatin, and the colors vary based on the dosage strength. The capsule body and cap are imprinted with pharmaceutical branding ink, which contains shellac, dehydrated alcohol, isopropyl alcohol, butyl alcohol, propylene glycol, purified water, strong ammonia, potassium hydroxide, and ferric oxide.

TEMODAR 5 mg: The green cap contains gelatin, titanium dioxide, iron oxide yellow, sodium lauryl sulfate, and FD&C Blue #2.

TEMODAR 20 mg: The yellow cap contains gelatin, sodium lauryl sulfate, and iron oxide yellow.

TEMODAR 100 mg: The pink cap contains gelatin, titanium dioxide, sodium lauryl sulfate, and iron oxide red.

TEMODAR 140 mg: The blue cap contains gelatin, sodium lauryl sulfate, and FD&C Blue #2.

TEMODAR 180 mg: The orange cap contains gelatin, iron oxide red, iron oxide yellow, titanium dioxide, and sodium lauryl sulfate.

TEMODAR 250 mg: The white cap contains gelatin, titanium dioxide, and sodium lauryl sulfate.

TEMODAR for injection:

Active ingredient: temozolomide.

Inactive ingredients: mannitol, L-threonine, polysorbate 80, sodium citrate dihydrate, and hydrochloric acid.

Distributed by: Merck Sharp & Dohme LLC, Rahway, NJ 07065, USA

For patent information: www.msd.com/research/patent

The trademarks depicted herein are owned by their respective companies.

Copyright © 1999-2023 Merck & Co., Inc., Rahway, NJ, USA, and its affiliates.
All rights reserved.

usppi-mk7365-mtl-2309r013
For more information, go to www.TEMODAR.com or call 1-877-888-4231.

This Patient Information has been approved by the U.S. Food and Drug Administration.

Revised: 9/2023

PRINCIPAL DISPLAY PANEL - 5 mg Capsule Sachet Carton

NDC 0085-3004-03

5 mg
per capsule

Temodar®
[temozolomide]
Capsules

For Oral Administration
WARNING: Hazardous Drug
Rx only

THIS PACKAGE CONTAINS
5 INDIVIDUAL SACHETS

Each Individual Sachet Contains
One Capsule Each

PRINCIPAL DISPLAY PANEL - 20 mg Capsule Sachet Carton

NDC 0085-1519-03

20 mg
per capsule

Temodar®
[temozolomide]
Capsules

For Oral Administration
WARNING: Hazardous Drug
Rx only

THIS PACKAGE CONTAINS
5 INDIVIDUAL SACHETS

Each Individual Sachet Contains
One Capsule Each

PRINCIPAL DISPLAY PANEL - 100 mg Capsule Sachet Carton

NDC 0085-1366-03

100 mg
per capsule

Temodar®
[temozolomide]
Capsules

For Oral Administration
WARNING: Hazardous Drug
Rx only

THIS PACKAGE CONTAINS
5 INDIVIDUAL SACHETS

Each Individual Sachet Contains
One Capsule Each

PRINCIPAL DISPLAY PANEL - 140 mg Capsule Sachet Carton

NDC 0085-1425-03

140 mg
per capsule

Temodar®
[temozolomide]
Capsules

For Oral Administration
WARNING: Hazardous Drug
Rx only

THIS PACKAGE CONTAINS
5 INDIVIDUAL SACHETS

Each Individual Sachet Contains
One Capsule Each

PRINCIPAL DISPLAY PANEL - 180 mg Capsule Sachet Carton

NDC 0085-1430-03

180 mg
per capsule

Temodar®
[temozolomide]
Capsules

For Oral Administration
WARNING: Hazardous Drug
Rx only

THIS PACKAGE CONTAINS
5 INDIVIDUAL SACHETS

Each Individual Sachet Contains
One Capsule Each

PRINCIPAL DISPLAY PANEL - 250 mg Capsule Sachet Carton

NDC 0085-1417-02

250 mg
per capsule

Temodar®
[temozolomide]
Capsules

For Oral Administration
WARNING: Hazardous Drug
Rx only

THIS PACKAGE CONTAINS
5 INDIVIDUAL SACHETS

Each Individual Sachet Contains
One Capsule Each

PRINCIPAL DISPLAY PANEL - 100 mg Vial Carton

NDC 0085-1381-01

Temodar®
[temozolomide]
for Injection

100 mg / VIAL

For Intravenous Infusion
after Reconstitution
WARNING: Hazardous Drug

Single-Dose Vial.
Discard unused portion.

Rx only